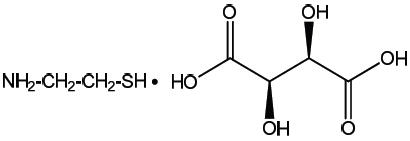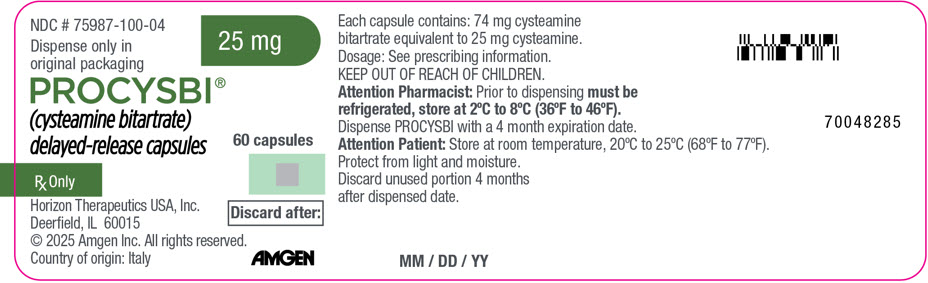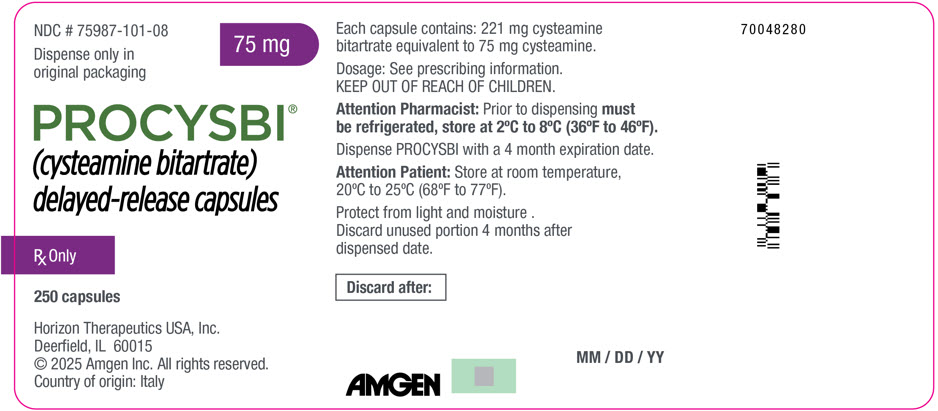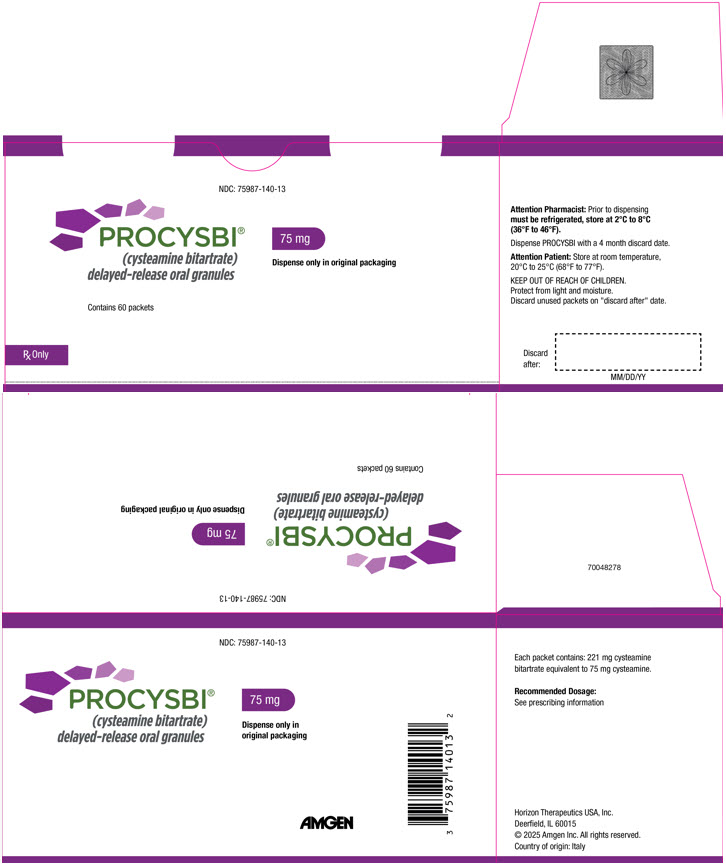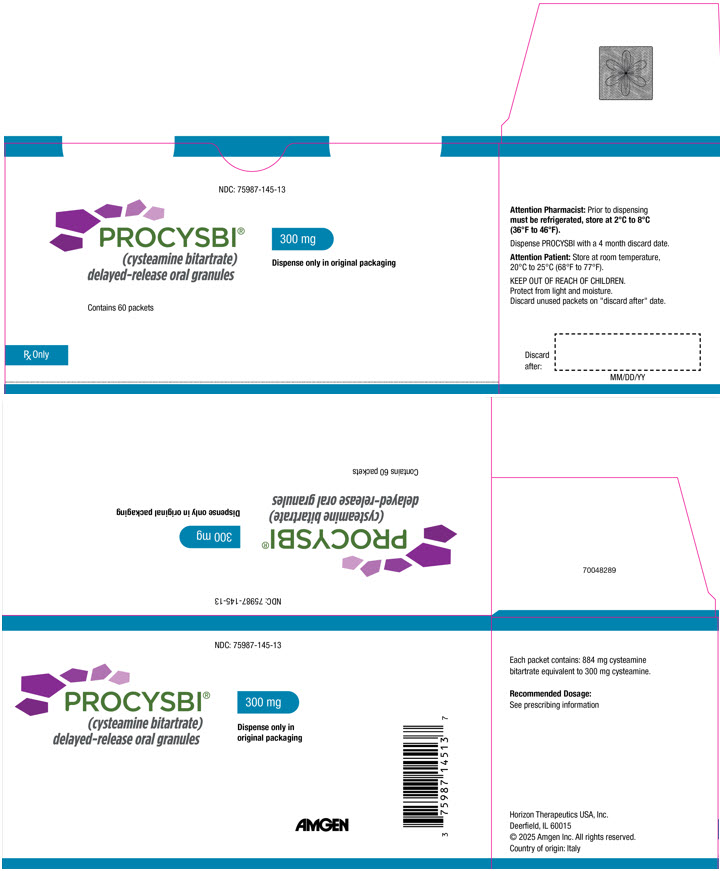 DRUG LABEL: PROCYSBI
NDC: 75987-100 | Form: CAPSULE, DELAYED RELEASE PELLETS
Manufacturer: Horizon Therapeutics USA, Inc.
Category: prescription | Type: HUMAN PRESCRIPTION DRUG LABEL
Date: 20250409

ACTIVE INGREDIENTS: CYSTEAMINE BITARTRATE 25 mg/1 1

HIGHLIGHTS OF PRESCRIBING INFORMATION

These highlights do not include all the information needed to use PROCYSBI safely and effectively. See Full Prescribing Information for PROCYSBI.
PROCYSBI® (cysteamine bitartrate) delayed-release capsules, for oral use
PROCYSBI® (cysteamine bitartrate) delayed-release oral granules
Initial U.S. Approval: 1994

RECENT MAJOR CHANGES

Warnings and Precautions, Fibrosing Colonopathy (5.4) | 02/2022

1 INDICATIONS AND USAGE

PROCYSBI is a cystine-depleting agent indicated for the treatment of nephropathic cystinosis in adults and pediatric patients 1 year of age and older. (1)

2 DOSAGE AND ADMINISTRATION

Recommended Dosage in Cysteamine-Naïve Patients

- See full prescribing information for weight-based dosing tables for the starting and maintenance dosage. (2.2)
- For initial intolerance, temporarily discontinue and then re-start PROCYSBI at a lower dosage and gradually increase to the maintenance dosage. (2.2)

Switching from Immediate-release Cysteamine to PROCYSBI

- Start with a total daily dose of PROCYSBI equal to the previous total daily dose of immediate-release cysteamine bitartrate. (2.3)

Dose Titration

- Adjust dose to achieve a therapeutic target white blood cell (WBC) cystine concentration. (2.4, 2.5)
- If a dose adjustment is required, increase the dosage by 10%. The maximum dosage is 1.95 grams/m^2 per day. (2.4)
- If adverse reactions occur, decrease the dosage. Some patients may be unable to achieve their therapeutic target. (2.4)

Preparation and Administration (2.6)

- Capsules: Swallow whole; do not crush or chew capsules or capsule contents. Take the capsules with fruit juice (except grapefruit juice) or water.
- Oral Granules: Do not crush or chew the granules. Sprinkle and mix the granules in applesauce, berry jelly or fruit juice (except grapefruit juice).
- For patients who cannot swallow the capsules or with gastrostomy tubes, see the full prescribing information on how to prepare and administer the capsules and oral granules.
- Administer PROCYSBI at least 1 hour before or 1 hour after medications containing bicarbonate or carbonate.
- Do not eat for at least 2 hours before and for at least 30 minutes after taking PROCYSBI. If unable to take PROCYSBI without eating, take with food but limit the amount of food to approximately 4 ounces (½ cup) 1 hour before through 1 hour after administration. Avoid high fat food close to dosing.
- Avoid drinking alcohol while taking PROCYSBI.

3 DOSAGE FORMS AND STRENGTHS

- Delayed-release capsules: 25 mg and 75 mg cysteamine (3)
- Delayed-release oral granules: 75 mg and 300 mg cysteamine in single-use packets (3)

4 CONTRAINDICATIONS

Hypersensitivity to penicillamine or cysteamine (4)

5 WARNINGS AND PRECAUTIONS

- Ehlers-Danlos-like Syndrome: Reduce dosage if skin and bone lesions occur. (5.1)
- Skin Rash: Discontinue if severe skin rash such as erythema multiforme bullosa or toxic epidermal necrolysis occurs. (5.2)
- Gastrointestinal (GI) Ulcers and Bleeding: Monitor for GI symptoms and consider decreasing the dose if severe symptoms occur. (5.3)
- Fibrosing Colonopathy: Evaluate patients with severe, persistent, and/or worsening abdominal symptoms for fibrosing colonopathy. If the diagnosis is confirmed, permanently discontinue PROCYSBI and switch to immediate-release cysteamine bitartrate capsules (5.4)
- Central Nervous System (CNS) Symptoms: Monitor for CNS symptoms; interrupt or reduce the dose for severe symptoms or those that persist or progress (5.5).
- Leukopenia and/or Elevated Alkaline Phosphatase Levels: Monitor white blood cell count and alkaline phosphatase levels; decrease or discontinue the dose until values revert to normal. (5.6)
- Benign Intracranial Hypertension: Monitor for signs and symptoms; interrupt or reduce the dose for signs/symptoms that persist, or discontinue if diagnosis is confirmed. (5.7)

6 ADVERSE REACTIONS

Most common adverse reactions in:

- Patients 6 years of age and older previously treated with cysteamine (≥5%) are: vomiting, nausea, abdominal pain, breath odor, diarrhea, skin odor, fatigue, rash, and headache. (6.1)
- Patients 1 year to less than 6 years naïve to cysteamine treatment (>10%) are: vomiting, gastroenteritis/viral gastroenteritis, diarrhea, breath odor, nausea, electrolyte imbalance and headache. (6.1)

To report SUSPECTED ADVERSE REACTIONS, contact Amgen Inc. at 1 800 77 AMGEN (1 800 772 6436) or FDA at 1-800-FDA-1088 or www.fda.gov/medwatch.

8 USE IN SPECIFIC POPULATIONS

Lactation: Breastfeeding is not recommended. (8.2)

FULL PRESCRIBING INFORMATION

1 INDICATIONS AND USAGE

PROCYSBI is indicated for the treatment of nephropathic cystinosis in adults and pediatric patients 1 year of age and older.

2 DOSAGE AND ADMINISTRATION

2.1 Important Dosing Instructions

- Initiate cysteamine treatment immediately after diagnosis of nephropathic cystinosis.
- Cysteamine-naïve Patients: Start PROCYSBI at a fraction of the maintenance dosage.
  - Patients 1 year to less than 6 years: Gradually increase the dosage, allowing a minimum of 2 weeks between adjustments [see Dosage and Administration (2.2)].
  - Patients 6 years of age and older: Gradually increase the dosage over 4 to 6 weeks until the maintenance dosage is achieved.
- Patients switching from immediate-release cysteamine: Start the total daily dosage of PROCYSBI at a dosage equal to the previous total daily dosage of immediate-release cysteamine [see Dosage and Administration (2.3)].
- If adverse reactions occur, decrease the PROCYSBI dosage.
- After the maintenance dosage of PROCYSBI is achieved: The dosage may need to be further increased to achieve a therapeutic target WBC cystine concentration. The maximum dosage of PROCYSBI is 1.95 grams/m^2 of body surface area per day [see Dosage and Administration (2.4, 2.5)].
- Round dose calculations to the nearest incremental dosage that can be administered using the available strengths of PROCYSBI delayed-release capsules or packets of oral granules. Only use whole capsules or entire contents of the packets.

2.2 Starting and Maintenance Dosing in Cysteamine-Naïve Patients

- Start treatment with a dosage equal to ⅙ to ¼ of the maintenance dosage.
- The maintenance dosage after initial dose escalation is 1.3 g/m^2 of body surface area per day divided into two doses given every 12 hours. Table 1 shows the recommended starting and maintenance dosages of PROCYSBI, converted from body-surface area to body weight.
  - Patients 1 year to less than 6 years: Increase the dosage in 10% increments to the maintenance dosage, while monitoring WBC cystine concentrations. Allow a minimum of 2 weeks between dosage adjustments [see Dosage and Administration (2.4, 2.5)]. If a patient achieves the therapeutic target WBC cystine concentration at a dosage below the recommended weight-based maintenance dosage, then stop dosage escalation and use the dosage as the patient's maintenance dosage.
  - Patients 6 years of age and older: Gradually increase the dosage over 4 to 6 weeks until the maintenance dosage is achieved.
- If a patient experiences initial intolerance, temporarily discontinue PROCYSBI and then re-start at a lower dosage and gradually increase dosage.

Table 1: Starting and Maintenance Dosage of PROCYSBI by Body Weight in Cysteamine-Naïve Patients 1 Year of Age and Older (Dosage Rounded Using Available Strengths of Capsules or Packets of Oral Granules)
Weight in kilograms | Starting PROCYSBI Dosage in mg every 12 hours, as a Fraction of the Maintenance Dosage |  | Maintenance PROCYSBI Dosage in mg every 12 hours [Higher dosages may be required to achieve target therapeutic WBC cystine concentration [see Dosage and Administration (2.4)].]
Weight in kilograms | ⅙ of dosage | ¼ of dosage | Maintenance PROCYSBI Dosage in mg every 12 hours [Higher dosages may be required to achieve target therapeutic WBC cystine concentration [see Dosage and Administration (2.4)].]
5 or less | 25 | 50 | 200
6 to 10 | 50 | 75 | 300
11 to 15 | 75 | 100 | 400
16 to 20 | 100 | 125 | 500
21 to 25 | 100 | 150 | 600
26 to 30 | 125 | 175 | 700
31 to 40 | 125 | 200 | 800
41 to 50 | 150 | 225 | 900
51 kg and greater | 175 | 250 | 1000

2.3 Switching Patients from Immediate-Release Cysteamine Bitartrate

- When switching patients from immediate-release cysteamine bitartrate to PROCYSBI, the starting total daily dose of PROCYSBI is equal to the previous total daily dose of immediate-release cysteamine bitartrate. Divide the total daily dose by two and administer every 12 hours.
- For patients who may experience temporary intolerance upon starting PROCYSBI, decrease the dosage and then gradually increase to the maintenance dosage.
- Measure the WBC cystine concentration two weeks after initiation of PROCYSBI [see Dosage and Administration (2.5)]. Adjust the PROCYSBI dosage as needed to achieve the therapeutic target WBC cystine concentration [see Dosage and Administration (2.4)]. The maximum dosage of PROCYSBI is 1.95 grams/m^2 per day.

2.4 Dosage Titration to Therapeutic Target WBC Cystine Concentration

- Measure WBC cystine concentration and titrate the PROCYSBI dosage as needed to achieve the therapeutic target WBC cysteine concentration [see Dosage and Administration (2.5)].
- If the measured WBC cystine concentration is above the target level for cystine depletion, consider the following before dose adjustment: adherence to medication and dosing interval, the timing between the last dose and the blood draw for the laboratory measurement, and the timing of PROCYSBI administration in relation to food or other administration instructions.
- If a dose adjustment is required, increase the dosage by 10%, rounded to nearest dosage that can be administered using the available strengths of capsules or packets of oral granules. For patients 1 year to less than 6 years of age, allow a minimum of two weeks between dose increments. The maximum dosage of PROCYSBI is 1.95 grams/m^2 per day.
- If adverse reactions occur, decrease the PROCYSBI dosage. Some patients may be unable to achieve their therapeutic target due to poor tolerability of PROCYSBI [see Warnings and Precautions (5), Adverse Reactions (6.1)].

2.5 Laboratory Monitoring

- WBC cystine concentration may be measured using the mixed leukocyte assay or by using assays for specific WBC subsets (e.g., granulocyte method). The methods used for measuring cystine and total protein content may also vary among individual laboratories [see Clinical Pharmacology (12.2)].
- Normal WBC cystine ranges and therapeutic target levels for cystine depletion depend upon the assay method used by the individual laboratory. WBC cystine values obtained from using different assay methods may not be comparable. Refer to the assay-specific therapeutic target for cystine depletion. When using the mixed leukocyte assay, the recommended target WBC cystine concentration is less than 1 nmol ½ cystine/mg protein.
- The recommended frequency of monitoring WBC cystine concentration is as follows:
  - Cysteamine-naïve patients 1 year to less than 6 years: Obtain measurement two weeks after initiation of PROCYSBI treatment and continue monitoring during dosage titration period until the therapeutic target WBC cystine concentration is achieved. Once the therapeutic target is achieved, continue monitoring monthly for 3 months, then quarterly for 1 year, and then twice-yearly, at a minimum.
  - Cysteamine-naïve patients greater than 6 years: Obtain measurement after reaching the maintenance PROCYSBI dosage, then monthly for 3 months, quarterly for 1 year, and then twice-yearly, at a minimum.
  - Patients switching from immediate-release cysteamine to PROCYSBI: Obtain measurement two weeks after initiation of PROCYSBI treatment and continue monitoring if further dosage titration is required to achieve therapeutic target WBC cystine concentration. Once the therapeutic target is achieved, continue monitoring quarterly for 6 months, then twice yearly, at a minimum.
- Obtain blood samples for WBC cystine concentration measurement 12 hours after the patient's last PROCYSBI dose, prior to administration of the next dose (i.e., trough concentration). In addition, it is important to accurately record the time of the last dose, the actual dose, and the time the blood sample was taken.

2.6 Preparation and Administration

- PROCYSBI delayed-release capsules:
  - Swallow capsules whole. Do not crush or chew capsules or capsule contents.
  - Take capsules with fruit juice (except grapefruit juice) or water.
  - For patients who cannot swallow the capsules, the capsules can be opened and the capsule contents sprinkled on and mixed in applesauce, berry jelly or fruit juice (except grapefruit juice) and administered orally, as described below.
  - For patients with a gastrostomy tube, the capsules can be opened and the capsule contents mixed in applesauce and administered via the gastrostomy tube, as described below.
- PROCYSBI delayed-release oral granules:
  - Do not crush or chew oral granules.
  - Sprinkle and mix the intact granules in applesauce, berry jelly or fruit juice (except grapefruit juice) and administered orally, as described below.
  - For patients with a gastrostomy tube, the oral granules can be mixed in applesauce and administered via a gastrostomy tube, as described below.
- Administer PROCYSBI at least 1 hour before or 1 hour after medications containing bicarbonate or carbonate [see Drug Interactions (7.1)].
- Do not eat for at least 2 hours before taking PROCYSBI and for at least 30 minutes after to maximize absorption. If patients are unable to take PROCYSBI without eating, take with food and limit the amount of food to approximately 4 ounces (½ cup) within 1 hour before taking PROCYSBI through 1 hour after taking PROCYSBI. Take PROCYSBI in a consistent manner in regard to food. Avoid high fat food close to dosing of PROCYSBI.
- Avoid drinking alcohol while taking PROCYSBI [see Drug Interactions (7.2)].

Oral Administration in Food or Liquid

Administration of PROCYSBI capsules or oral granules with foods and liquids not included below has not been studied clinically and is not recommended.

Administration in Applesauce or Berry Jelly:

1. Place approximately 4 ounces (½ cup) or a smaller amount that can be consumed in one feeding of either applesauce or berry jelly into a clean container.
2. Open the capsule(s) or packet(s).
3. Sprinkle all the intact granules that are inside the capsule(s) or packet(s) on applesauce or berry jelly.
4. Mix the granules with the applesauce or berry jelly. Do not crush the granules.
5. Consume the entire contents within 30 minutes of mixing. Do not chew the granules. Do not save the applesauce or berry jelly and granules for later use.

Administration in Fruit Juice (except grapefruit juice):

1. Pour approximately 4 ounces (½ cup) of fruit juice into a clean cup.
2. Open the capsule(s) or packet(s).
3. Sprinkle all the intact granules into the juice.
4. Gently stir until mixed. Do not crush the granules.
5. Drink the entire contents within 30 minutes of mixing. Do not chew the granules. Do not save the fruit juice and granules mixture for later use.

Administration in Applesauce via a Gastrostomy (G) Tube (14 French or larger)

A bolus (straight) feeding tube is recommended.

1. Flush the gastrostomy tube button first with 5 mL of water to clear the button.
2. Open the capsule(s) or packet(s) and empty the granules into a clean container with approximately 4 ounces (½ cup) of applesauce. Use only strained applesauce with no chunks. A minimum of 1 ounce (⅛cup) of applesauce may be used for children 25 kg or less starting PROCYSBI at a dose of 1 or 2 capsules or packets.
3. Mix the intact granules into the applesauce. Do not crush the granules.
4. Draw up the mixture into a syringe. Keep the feeding tube horizontal during administration and apply rapid and steady pressure (10 mL/10 seconds) to dispense the syringe contents into the tube within 30 minutes of preparation.
5. Repeat step 3 until all of the mixture is administered. Do not save the applesauce and granule mixture for later use.
6. Draw up a minimum of 10 mL of fruit juice or water into another syringe, swirl gently, and flush the tube.

Missed Doses

- If a dose is missed, take the dose as soon as possible up to 8 hours after the scheduled time. However, if a dose is missed and the next scheduled dose is due in less than 4 hours, do not take the missed dose and take the next dose at the usual scheduled time. Do not take 2 doses at one time to make up for a missed dose.

3 DOSAGE FORMS AND STRENGTHS

PROCYSBI delayed-release capsules:

- 25 mg cysteamine: the capsules have a light blue opaque cap imprinted with "PRO" in white ink and a light blue opaque body imprinted with "25 mg" in white ink.
- 75 mg cysteamine: the capsules have a dark blue opaque cap imprinted with "PRO" in white ink and a light blue opaque body imprinted with "75 mg" in white ink.

PROCYSBI delayed-release oral granules:

- 75 mg cysteamine: white to off-white granules in single-use packets
- 300 mg cysteamine: white to off-white granules in single-use packets

4 CONTRAINDICATIONS

The use of PROCYSBI is contraindicated in patients with a serious hypersensitivity reaction, including anaphylaxis, to penicillamine or cysteamine.

5 WARNINGS AND PRECAUTIONS

5.1 Ehlers-Danlos-like Syndrome

Skin and bone lesions that resemble clinical findings for Ehlers-Danlos-like syndrome have been reported in patients treated with high doses of immediate-release cysteamine bitartrate or other cysteamine salts. These include molluscoid pseudotumors (purplish hemorrhagic lesions), skin striae, bone lesions (including osteopenia, compression fractures, scoliosis and genu valgum), leg pain, and joint hyperextension. One patient on immediate-release cysteamine bitartrate with serious skin lesions subsequently died of acute cerebral ischemia with marked vasculopathy. Monitor patients for development of skin or bone lesions and interrupt PROCYSBI dosing if patients develop these lesions. PROCYSBI may be restarted at a lower dose under close supervision, then slowly increase to the appropriate therapeutic dose [see Dosage and Administration (2.1, 2.4)].

5.2 Skin Rash

Severe skin rashes such as erythema multiforme bullosa or toxic epidermal necrolysis have been reported in patients receiving immediate-release cysteamine bitartrate. If severe skin rashes develop, permanently discontinue use of PROCYSBI [see Contraindications (4)].

5.3 Gastrointestinal Ulcers and Bleeding

Gastrointestinal (GI) ulceration and bleeding have been reported in patients receiving immediate-release cysteamine bitartrate. GI tract symptoms including nausea, vomiting, anorexia and abdominal pain, sometimes severe, have been associated with cysteamine. If severe GI tract symptoms develop, consider decreasing the dose of PROCYSBI [see Dosage and Administration (2.1, 2.4)].

5.4 Fibrosing Colonopathy

Fibrosing colonopathy, including colonic stricture formation, has been reported with postmarketing use of PROCYSBI in pediatric and young adult patients with nephropathic cystinosis. Some of these patients had been treated with PROCYSBI for prolonged periods of time. Reported symptoms include: abdominal pain, vomiting, bloody or persistent diarrhea, and fecal incontinence. Evaluate patients with severe, persistent, and/or worsening abdominal symptoms for fibrosing colonopathy. If the diagnosis is confirmed, permanently discontinue PROCYSBI and switch to immediate-release cysteamine bitartrate capsules. An association between methacrylic acid-ethyl acrylate copolymer (an inactive ingredient in PROCYSBI) and fibrosing colonopathy cannot be ruled out.

5.5 Central Nervous System Symptoms

Central Nervous System (CNS) symptoms such as seizures, lethargy, somnolence, depression, and encephalopathy have been associated with immediate-release cysteamine. Neurological complications have also been described in some patients with cystinosis who have not been treated with cysteamine. Carefully evaluate and monitor patients who develop CNS symptoms. Interrupt medication or adjust the dose as necessary for patients with severe symptoms or with symptoms that persist or progress. Inform patients that PROCYSBI may impair their ability to perform tasks such as driving or operating machinery.

5.6 Leukopenia and/or Elevated Alkaline Phosphatase Levels

Cysteamine has been associated with reversible leukopenia and elevated alkaline phosphatase levels. Monitor white blood cell counts and alkaline phosphatase levels. If tests values remain elevated, consider decreasing the dose or discontinuing the drug until values revert to normal.

5.7 Benign Intracranial Hypertension

Benign intracranial hypertension (pseudotumor cerebri; PTC) and/or papilledema have been reported in patients receiving immediate-release cysteamine bitartrate treatment. Monitor patients for signs and symptoms of PTC, including headache, tinnitus, dizziness, nausea, diplopia, blurry vision, loss of vision, pain behind the eye or pain with eye movement. If signs/symptoms persist, interrupt dosing or decrease the dose and refer the patient to an ophthalmologist. If the diagnosis is confirmed, permanently discontinue use of PROCYSBI.

6 ADVERSE REACTIONS

The following adverse reactions are also discussed in other sections of the labeling:

- Ehlers-Danlos-like Syndrome [see Warnings and Precautions (5.1)]
- Skin Rash [see Warnings and Precautions (5.2)]
- Gastrointestinal (GI) Ulcers and Bleeding [see Warnings and Precautions (5.3)]
- Fibrosing Colonopathy [see Warnings and Precautions (5.4)]
- Central Nervous System Symptoms [see Warnings and Precautions (5.5)]
- Leukopenia and/or Elevated Phosphatase Levels [see Warnings and Precautions (5.6)]
- Benign Intracranial Hypertension [see Warnings and Precautions (5.7)]

6.1 Clinical Trials Experience

Because clinical trials are conducted under widely varying conditions, adverse reaction rates observed in the clinical trials of a drug cannot be directly compared with rates in the clinical trials of another drug and may not reflect the rates observed in clinical practice.

The data described below reflect exposure to cysteamine in 345 patients with nephropathic cystinosis (246 patients receiving immediate-release cysteamine as cysteamine hydrochloride or phosphocysteamine, and 80 patients receiving PROCYSBI) in open-label clinical trials.

Clinical Trials Experience with PROCYSBI in Patients Switched from Immediate-Release Cysteamine Bitartrate

Sixty-two patients with nephropathic cystinosis (38 males and 24 females) received PROCYSBI in two clinical trials at doses ranging from 0.29 grams/m^2 per day to 2.19 grams/m^2 per day [see Clinical Studies (14.2)]. All patients were switched from immediate-release cysteamine to PROCYSBI. Forty-three patients, ages 6 to 26 years old, received PROCYSBI in an 8-week, open-label, randomized, cross-over trial comparing PROCYSBI to immediate-release cysteamine bitartrate. Forty of 43 patients continued PROCYSBI treatment in an open-label extension trial (36 patients were treated with PROCYSBI for longer than 2 years, and 20 patients were treated for longer than 5 years). An additional 19 patients (6 renal transplanted patients and 13 patients aged 2 to 6 years) were enrolled directly into this trial (12 patients were treated with PROCYSBI for longer than 2 years, and 9 patients were treated for longer than 5 years).

In the open-label, randomized, cross-over trial, a higher incidence of adverse reactions was reported in patients during the PROCYSBI treatment period compared with the immediate-release cysteamine bitartrate treatment period (see Table 2). Other significant adverse reactions reported during clinical trials included hypersensitivity reactions, including anaphylaxis.

Table 2: Adverse Reactions in ≥5% of Patients with Nephropathic Cystinosis in a Randomized, Cross-Over Trial
Adverse Reaction | Immediate-Release Cysteamine | PROCYSBI
Adverse Reaction | (n = 41) % | (n = 43) %
Vomiting/emesis | 12 | 19
Nausea | 7 | 16
Abdominal pain/discomfort | 0 | 14
Headache | 0 | 9
Dizziness | 0 | 5
Anorexia/loss of appetite | 5 | 2

In the open-label extension trial (N=59), the most commonly reported adverse reactions (>15%) were vomiting, headache, diarrhea, nausea, conjunctivitis, influenza, gastroenteritis, nasopharyngitis, abdominal pain, dehydration, ear infection, upper respiratory tract infection, fatigue, arthralgia, cough, and pain in extremity.

Clinical Trials Experience with PROCYSBI in Cysteamine-Naïve Patients

Seventeen cysteamine-naïve patients (fifteen patients between the ages of 1 and 5 years, one 9-year old and one 22-year old) received PROCYSBI in an open-label clinical trial [see Clinical Studies (14.2)]. Serious adverse reactions occurring in at least 2 patients (>10%) were: gastroenteritis/viral gastroenteritis (n=6), vomiting (n=4), and electrolyte imbalance (n=2). Three patients with serious adverse reactions of gastroenteritis also had dehydration. Common adverse reactions reported at a frequency of >10% (occurring in at least 2 patients) are shown in Table 3.

Table 3: Adverse Reactions in >10% of Patients with Nephropathic Cystinosis Naïve to Cysteamine Treatment in an Open-Label Trial
Adverse Reaction | PROCYSBI N = 17 n (%)
Vomiting | 13 (77)
Gastroenteritis/viral gastroenteritis | 9 (53)
Diarrhea | 6 (35)
Breath odor | 4 (24)
Nausea | 3 (18)
Electrolyte imbalance | 2 (12)
Headache | 2 (12)

Clinical Trials Experience with Immediate-Release Cysteamine

The most frequent adverse reactions involved the gastrointestinal and central nervous systems and were especially prominent at the initiation of cysteamine therapy. Most patients were able to resume therapy at lower doses. The most common reactions (>5%) were vomiting, anorexia, fever, diarrhea, lethargy, and rash. Other adverse reactions included nausea, bad breath, abdominal pain, headache, dizziness, and urticaria.

Withdrawals due to intolerance, vomiting, anorexia, lethargy, and fever occurred more frequently in those patients receiving 1.95 grams/m^2 per day as compared with 1.3 grams/m^2 per day of immediate-release cysteamine bitartrate.

6.2 Postmarketing Experience

The following adverse reactions have been identified during post-approval use of cysteamine bitartrate. Because these reactions are reported voluntarily from a population of uncertain size, it is not always possible to reliably estimate their frequency or establish a causal relationship to drug exposure.

- Musculoskeletal: Joint hyperextension, leg pain, osteopenia, compression fracture, scoliosis, genu valgum [see Warnings and Precautions (5.1)].
- Skin: Erythema multiforme bullosa, toxic epidermal necrolysis, Ehlers-Danlos-like syndrome, molluscoid pseudotumors, skin striae, skin fragility [see Warnings and Precautions (5.1, 5.2)].
- Gastrointestinal: Fibrosing colonopathy reported with PROCYSBI [see Warnings and Precautions (5.4)].
- Central Nervous System: seizures, lethargy, somnolence, depression and encephalopathy [see Warnings and Precautions (5.5)], benign intracranial hypertension (or PTC) and/or papilledema [see Warnings and Precautions (5.7)].

7 DRUG INTERACTIONS

7.1 Drugs that Increase Gastric pH

Drugs that increase the gastric pH (e.g., medications containing bicarbonate or carbonate) may alter the pharmacokinetics of cysteamine due to the premature release of cysteamine from PROCYSBI and increase WBC cystine concentration. Concomitant administration of 20 mg omeprazole did not affect the pharmacokinetics of cysteamine when PROCYSBI was administered with 240 mL of orange juice or with 240 mL of water [see Clinical Pharmacology (12.3)]. Monitor WBC cystine concentration when drugs that increase the gastric pH are concomitantly used [see Dosage and Administration (2.5)].

7.2 Use with Alcohol

Consumption of alcohol with PROCYSBI may increase the rate of cysteamine release and/or adversely alter the pharmacokinetic properties, as well as the effectiveness and safety of PROCYSBI. Therefore, do not consume alcoholic beverages during treatment with PROCYSBI [see Dosage and Administration (2.6)].

7.3 Other Medications Used for the Management of Fanconi Syndrome

PROCYSBI can be administered with other electrolyte and mineral replacements necessary for management of Fanconi syndrome, as well as vitamin D and thyroid hormone.

8 USE IN SPECIFIC POPULATIONS

8.1 Pregnancy

Risk Summary

There are no available data on PROCYSBI use in pregnant women to inform any drug-associated risks for birth defects or miscarriage [see Data]. Cysteamine (administered as cysteamine bitartrate) was teratogenic and fetotoxic in rats at doses less than the recommended human maintenance dose.

The background risk of major birth defects and miscarriage for the indicated population is unknown. In the U.S. general population, the estimated background risk of major birth defects and miscarriage in clinically recognized pregnancies is 2 to 4% and 15 to 20%, respectively. Advise pregnant women of the potential risk to a fetus.

Data

Animal Data

Embryo-fetal development studies were conducted in rats using oral administration of cysteamine bitartrate, with a dose range of 37.5 to 150 mg/kg per day of cysteamine equivalent (about 0.2 to 0.7 times the recommended human maintenance dose based on body surface area). Cysteamine bitartrate was fetotoxic and produced adverse developmental effects. Observed teratogenic findings were cleft palate, kyphosis, heart ventricular septal defects, microcephaly and exencephaly.

8.2 Lactation

Risk Summary

There is no information on the presence of cysteamine in human milk, the effects on the breast-fed infant, or the effects on milk production. Cysteamine is present in the milk of lactating rats [see Data]. Because of the potential for serious adverse reactions in breastfed infants from cysteamine, breastfeeding is not recommended.

Data

A decrease in survival occurred in neonatal rats nursed by mothers receiving cysteamine [see Nonclinical Toxicology (13)].

8.4 Pediatric Use

The safety and effectiveness of PROCYSBI have been established in pediatric patients 1 year of age and older for the treatment of nephropathic cystinosis. Use of PROCYSBI is supported by evidence from patients switched to PROCYSBI from immediate-release cysteamine bitartrate in two trials: an open-label, randomized, cross-over trial in adults and pediatric patients aged 6 years and older (n=43) and an open-label extension trial in pediatric patients aged 2 years and older (n=59). Another open-label trial was conducted in cysteamine naïve pediatric patients 1 year to less than 6 years of age (n=15) [see Clinical Trials (14.2)]. The safety profile in pediatric patients was similar to adults. In patients less than 6 years of age, vomiting occurred in 12/15 cysteamine treatment naïve patients compared to 11/13 patients switched from immediate-release cysteamine to PROCYSBI.

The safety and effectiveness of PROCYSBI have not been established in patients less than 1 year of age.

8.5 Geriatric Use

No studies with PROCYSBI have been conducted in geriatric patients.

10 OVERDOSAGE

One case of overdosing with PROCYSBI has been reported. A 16-year-old male patient suffered nausea and vomiting after he mistakenly took a second dose of PROCYSBI 30 minutes after his usual dose.

Two cases of overdosing with immediate-release cysteamine bitartrate have been reported in two patients. In the first case, the patient immediately vomited after ingesting an unknown dose and did not develop any symptoms. The second case involved an accidental ingestion of a 200 to 250 mg/kg dose by a healthy 13-month-old child. Vomiting and dehydration were experienced. The child was hospitalized and fluids were administered. The patient fully recovered from the overdosing.

Should overdosing occur, the respiratory and cardiovascular systems should be supported appropriately. No specific antidote is known. Hemodialysis may be considered since cysteamine is poorly bound to plasma proteins.

11 DESCRIPTION

PROCYSBI, for oral administration, is a cystine-depleting agent that lowers the cystine content of cells in patients with nephropathic cystinosis, an inherited defect of lysosomal transport.

PROCYSBI contains the bitartrate salt of cysteamine. The chemical name for cysteamine bitartrate is ethanethiol, 2-amino, (2R,3R)-2,3-dihydroxybutanedioate (1:1) (salt). Cysteamine bitartrate is a highly water soluble white powder with a molecular weight of 227.24 and the molecular formula C2H7NS ∙ C4H6O6. It has the following chemical structure:

Each PROCYSBI delayed-release capsule contains either 25 mg cysteamine (equivalent to 74 mg cysteamine bitartrate) or 75 mg cysteamine (equivalent to 221 mg cysteamine bitartrate).

Each packet of PROCYSBI delayed-release oral granules contains either 75 mg cysteamine (equivalent to 221 mg cysteamine bitartrate) or 300 mg cysteamine (equivalent to 884 mg cysteamine bitartrate).

PROCYSBI delayed release granules contain the following inactive ingredients: Eudragit® L 30 D-55 (methacrylic acid-ethyl acrylate copolymer), hypromellose, microcrystalline cellulose, purified water, sodium lauryl sulfate, talc, and triethyl citrate. Additionally the capsule shell contains the following inactive ingredients: gelatin, ink (blue and white), and titanium dioxide.

12 CLINICAL PHARMACOLOGY

12.1 Mechanism of Action

Cysteamine is an aminothiol that participates within lysosomes in a thiol-disulfide interchange reaction converting cystine into cysteine and cysteine-cysteamine mixed disulfide, both of which can exit the lysosome in patients with cystinosis.

12.2 Pharmacodynamics

Normal individuals and persons heterozygous for cystinosis have WBC cystine concentrations of less than 0.2 and usually below 1 nmol ½ cystine/mg protein, respectively, when measured using the mixed leukocyte assay. Untreated patients with nephropathic cystinosis have elevations of WBC cystine concentration above 2 nmol ½ cystine/mg protein.

After the administration of a single dose of PROCYSBI, peak concentrations of cysteamine were observed at 3 hours post-dose. The nadir of WBC cystine closely followed the peak concentrations at 3.5 hours post-dose, and returned to baseline WBC concentrations at 12 hours-post dose. The cystine concentration in WBC lysate was measured with LC/MS/MS and total protein content in human WBC lysate was measured using the bicinchoninic acid (BCA) assay. A correction factor was applied to the total protein content for the difference in results from the Lowry method. The cystine concentration in nmol ½ cystine/mg protein was calculated by multiplying nmol cystine/mg protein by 2 [see Dosage and Administration (2.5)].

12.3 Pharmacokinetics

The pharmacokinetics of cysteamine with administration of PROCYSBI were evaluated in 43 patients age ranged from 6 to 26 years (mean age 12 years) with cystinosis and with an estimated glomerular filtration rate of greater than 30 mL/minutes/1.73 m2. Table 4 shows the mean pharmacokinetic parameters for PROCYSBI and immediate-release cysteamine bitartrate at steady state. The mean (± SD) dose for PROCYSBI was 656 ± 144 mg/m2 (given every 12 hours) and for immediate-release cysteamine bitartrate was 404 ± 88 mg/m2 (given every 6 hours).

Table 4: Pharmacokinetic parameters for cysteamine at steady state* after administration of PROCYSBI or immediate-release cysteamine bitartrate
 | Immediate-release cysteamine bitartrate given every 6 hours | PROCYSBI given every 12 hours
Cmax (mg/L) | 2.7 ± 1.4 | 3.6 ± 1.8
AUC0-6h (min*mg/L) | 351 ± 153 | NA
AUC0-12h (min*mg/L) | NA | 726 ± 339
AUCinf (min*mg/L) | 380 ± 157 | 785 ± 358
Tmax (min) | 73 ± 31 | 188 ± 88
t½ (min) | 90 ± 24 | 253 ± 403
CL/F (L/min) | 1.4 ± 0.8 | 1.2 ± 0.8
Vd/F (L) | 198 ± 159 | 382 ± 404

Absorption

The pharmacokinetics of cysteamine with administration of PROCYSBI are consistent with a delayed-release formulation; the mean Tmax for cysteamine was 188 minutes with PROCYSBI compared with 73 minutes for immediate-release cysteamine bitartrate.

The mean plasma cysteamine peak and AUC were similar when a single PROCYSBI dose of 600 mg was administered with 240 mL orange juice or with 240 mL water. The systemic exposure to cysteamine was similar when PROCYSBI was administered with orange juice as a whole capsule and sprinkled in applesauce in the fasted state. In a food effect study conducted in healthy subjects (n=20), administration of a meal 30 minutes following PROCYSBI administration (intact capsules) decreased Cmax by 34% and AUC0-t by 32% compared to administration of a meal 2 hours post-dose [see Dosage and Administration (2.6)].

Distribution

Cysteamine was moderately bound to human plasma proteins, predominantly to albumin, with mean protein binding of about 52%. Plasma protein binding was independent of concentration over the concentration range achieved clinically with the recommended doses. The volume of distribution (Vd/F) was 382 L for PROCYSBI compared with 198 L for immediate-release cysteamine bitartrate.

Elimination

After each dose of PROCYSBI the cysteamine concentration in the blood continues to decline for approximately 30 minutes and the WBC cystine concentration increases accordingly.

The apparent clearance (Cl/F) of cysteamine was similar between PROCYSBI (1.2 ± 0.8 L/min) and immediate-release cysteamine bitartrate (1.4 ± 0.8 L/min).

The half-life was 253 minutes for PROCYSBI and 90 minutes for immediate-release cysteamine bitartrate.

Specific Populations

Pediatric patients 1 year to less than 6 years of age

The pharmacokinetics of cysteamine with administration of PROCYSBI at steady state were evaluated in 11 cysteamine treatment naïve patients between the ages of 1 and 5 years of age with nephropathic cystinosis. A mean (± SD) Cmax of 1.26 ± 0.86 mg/L was reached at an average Tmax of 199 ± 138 minutes and the mean (± SD) dose was 242 ± 93 mg/m^2. The mean exposure was calculated to be 206 ± 113 minutes*mg/L (AUClast) and 231 ± 123 minutes*mg/L (AUCinf). The mean CLss/F was estimated to be 0.69 ± 0.37 L/minutes with an average half-life (t½) of 270 ± 56 minutes. Overall, the pharmacokinetics in patients between the ages of 1 and 5 years of age is comparable with those in older children and adults.

Patients with Renal Impairment

The pharmacokinetics of cysteamine with administration of a single oral dose of 600 mg PROCYSBI were evaluated in non-cystinosis subjects with renal impairment and healthy subjects with normal renal function (eGFR >90 mL/min/1.73m^2) matched for age, body mass index and sex.

The mean AUCinf and mean Cmax for cysteamine were 8%, and 3% lower, respectively, in subjects with mild renal impairment (eGFR 60 to 89 mL/min/1.73m^2) compared to healthy subjects. In subjects with moderate renal impairment (eGFR 30 to 59 mL/min/1.73m^2) and severe renal impairment (≤29 mL/min/1.73m^2), the mean AUCinf was 49% and 35% higher and the mean Cmax was 27% and 11% higher, respectively compared to healthy subjects. The mean t½ was 7 hours, 8.3 hours, and 8.8 hours in subjects with mild, moderate, and severe renal impairment, respectively and ranged from 6.6 to 7.5 hours in healthy subjects. The mean CL/F was 1.57, 1.08, and 1.09 L/min in mild, moderate, and severe renal impairment subjects compared to 1.40 to 1.60 L/min in healthy subjects.

In subjects with end-stage renal disease receiving 4 hours of hemodialysis, the geometric mean Cmax and AUCinf of cysteamine was 60% higher when PROCYSBI was administered 3 hours before hemodialysis, and 22% higher when administered 1 hour after completion of hemodialysis compared to healthy subjects. Approximately 4.3% (25.6 mg) of the 600 mg PROCYSBI dose was removed from the body with hemodialysis. The apparent clearance of cysteamine in subjects who received PROCYSBI before hemodialysis was approximately 65 mL/min.

The increased exposure to cysteamine in patients with renal impairment compared to healthy subjects is not considered to be clinically meaningful.

Drug Interaction Studies

An in vitro study indicates cysteamine bitartrate is not an inhibitor of CYP enzymes (CYP1A2, CYP2A6, CYP2B6, CYP2C8, CYP2C9, CYP2C19, CYP2D6, CYP2E1, and CYP3A4). The potential for cysteamine to affect the pharmacokinetics of other drugs via these enzymes is low.

Omeprazole

The effect of concomitant omeprazole on the pharmacokinetics of cysteamine was evaluated following co-administration of single PROCYSBI dose of 600 mg with 20 mg of omeprazole in comparison to administration of PROCYSBI alone in healthy subjects in two separate studies. In both studies omeprazole was dosed once daily for 5 days before co-administration with PROCYSBI and single dose PROCYSBI was given either with 240 mL orange juice in one study or with 240 mL water in another study. The pharmacokinetic parameters of cysteamine were not significantly different when PROCYSBI was administered with omeprazole compared to when PROCYSBI was administered alone, regardless whether PROCYSI was administered with orange juice or water [see Dosage and Administration (2.6), Drug Interactions (7.1)].

13 NONCLINICAL TOXICOLOGY

13.1 Carcinogenesis, Mutagenesis, Impairment of Fertility

Cysteamine has not been tested for its carcinogenic potential in long-term animal studies.

PROCYSBI was not mutagenic in the Ames test. It produced a negative response in an in-vitro sister chromatid exchange assay in human lymphocytes, but a positive response in a similar assay in hamster ovarian cells.

Repeat breeding reproduction studies were conducted in male and female rats. Cysteamine was found to have no effect on fertility and reproductive performance at an oral dose of 75 mg/kg per day (450 mg/m^2 per day, 0.4 times the recommended human dose based on body surface area). At an oral dose of 375 mg/kg per day (2250 mg/m^2 per day, 1.7 times the recommended human maintenance dose based on body surface area), it reduced the fertility of the adult rats and the survival of their offspring.

14 CLINICAL STUDIES

14.1 Clinical Trials with Immediate-Release Cysteamine

Efficacy of immediate-release cysteamine bitartrate was demonstrated in open-label clinical trials of cysteamine hydrochloride and phosphocysteamine.

An open-label clinical trial of cysteamine hydrochloride was conducted in 94 pediatric patients (mainly from the United States) with nephropathic cystinosis. Patients were treated with increasing doses of cysteamine hydrochloride (mean dose 54 mg/kg per day) to attain WBC cystine concentrations of less than 2 nmol ½ cystine/mg protein 5 to 6 hours post-dose. The clinical outcomes were compared with a historical control group of 17 pediatric patients who had been in the placebo group of a randomized placebo-controlled trial of ascorbic acid. Cysteamine-treated patients had been diagnosed at a mean age of 22 months and had a mean age of 46 months old at study entry; placebo patients had been diagnosed at about 29 months and had a mean age of about 52 months old at trial entry. The principal measures of effectiveness were serum creatinine and calculated creatinine clearance and growth (height).

The average median WBC cystine concentration during treatment was 1.7 ± 0.2 nmol ½ cystine/mg protein. There were 70 cysteamine-treated patients with a baseline serum creatinine of less than 2 mg/dL who were followed for at least 1 year, and 17 placebo patients. Twelve of the 94 cysteamine-treated patients required early dialysis or renal transplant. Median follow-up of cysteamine patients was over 32 months, and 20% were followed more than 5 years. Median follow-up of the placebo group was 20 months; only 1 patient was followed more than 24 months. Glomerular function among cysteamine-treated patients was maintained over time. Placebo-treated patients experienced a gradual rise in serum creatinine. Renal tubular function was not affected by treatment.

Calculated creatinine clearances were evaluated for two groups of pediatric patients, one with poor WBC cystine depletion (defined as median WBC cystine concentrations greater than 3 nmol ½ cystine/mg protein or WBC cystine concentrations not measured at least 2 times per year) and one with good WBC cystine depletion. The final mean creatinine clearance of the good depletion group was 20.8 mL/min/1.73 m^2 greater than the mean for the poor-depletion group.

Height-for-age measurements of treated patients were compared with height-for-age measurements of 143 patients initially screened for inclusion in the trial. Patients on treatment maintained growth (i.e., did not show increasing growth failure compared with normal scales) although growth velocity did not increase enough to allow patients to catch up to age norms for height.

In another open-label clinical trial, 46 patients who had completed the clinical trial of cysteamine hydrochloride (averaging 6.5 years of treatment) and 93 treatment naïve patients were treated with either cysteamine hydrochloride or phosphocysteamine (patient's choice). Patients had cystinosis diagnosed by elevated WBC cystine (mean 3.63 nmol ½ cystine/mg). Newly enrolled patients and the 46 continuing patients were required to have serum creatinine less than 3 mg/dL and 4 mg/dL, respectively. Patients were randomized to doses of 1.3 or 1.95 grams/m^2 per day and stratified according to whether the serum creatinine was above 1.2 mg/dL or not. Doses could be raised if WBC cystine concentrations were approximately 2 nmol ½ cystine/mg protein and lowered due to intolerance. The mean age of the newly enrolled patients was about 49 months for the cysteamine group and about 34 months for the phosphocysteamine group. The mean age of the patients in the long-term follow-up group was about 9 years.

Mean doses were 1.27 grams/m^2 per day and 1.87 grams/m^2 per day in the two groups and WBC cystine concentrations averaged 1.72 ± 1.65 nmol ½ cystine/mg protein and 1.86 ± 0.92 nmol ½ cystine/mg protein in the 1.3 grams/m^2 per day and 1.95 grams/m^2 per day in the two groups, respectively. In new patients, serum creatinine was essentially unchanged over the period of follow-up (about half of the patients were followed for 24 months) and phosphocysteamine and cysteamine hydrochloride had similar effects. The long-term follow-up group also had essentially no change in renal function (almost 80% were followed at least 2 years). In four studies of patients with untreated cystinosis, renal death (need for transplant or dialysis) occurred at median age of less than 10 years. Both new patients and patients in the long-term follow-up group maintained height (although they did not catch up from baseline). There was no apparent difference in height maintenance between the two doses.

14.2 Clinical Trials with PROCYSBI

Multi-Center, Open-Label, Randomized Clinical Trial in Patients Receiving Immediate-Release Cysteamine Bitartrate

A clinical trial comparing immediate-release cysteamine bitartrate and PROCYSBI was conducted in 43 (40 pediatric and 3 adult) patients with nephropathic cystinosis (Study RP103-03; NCT01000961). Patient age ranged from 6 to 26 years (mean age 12 years) and 56% were male. Patients with WBC cystine concentrations greater than 2 nmol ½ cystine/mg protein (measured using the mixed leukocyte assay) and estimated glomerular filtration rate (eGFR corrected for body surface area) less than 30 mL/minute/1.73 m^2 at the time of screening were excluded from the trial. Prior to randomization, patients were to be on a stable dose of immediate-release cysteamine bitartrate administered every six hours. PROCYSBI dose adjustments of up to approximately 100% of the total daily dose of immediate-release cysteamine bitartrate were allowed by trial criteria. The average total daily dose of PROCYSBI for patients completing the clinical trial was approximately 91% of the average total daily dose of immediate-release cysteamine bitartrate for patients at trial entry.

This trial demonstrated that at steady-state, PROCYSBI administered every 12 hours was non-inferior to immediate-release cysteamine bitartrate administered every 6 hours with respect to the depletion of WBC cystine concentrations (Table 5). Using a linear mixed effects statistical analysis model, the least-square-mean value of WBC cystine was 0.52 ± 0.06 nmol ½ cystine/mg protein after 12 hours under PROCYSBI and 0.44 ± 0.06 nmol ½ cystine/mg protein after 6 hours under immediate-release cysteamine; a difference of 0.08 ± 0.03 nmol ½ cystine/mg protein (95.8% Confidence Interval = 0.01 to 0.15).

Table 5: Comparison of WBC cystine concentrations in open-label, randomized, cross-over clinical trial participants, who were on a stable dose of immediate-release cysteamine prior to randomization, with WBC cystine less than 2 nmol ½ cystine/mg protein throughout the trial [Per–Protocol (PP) Population (N=39)]
 | Immediate-release cysteamine bitartrate | PROCYSBI
WBC cystine concentration in nmol ½ cystine/mg protein (LS Mean ± SE) | 0.44 ± 0.06 | 0.52 ± 0.06
Difference in Treatment effect (LS mean ± SE) [95.8% CI; p-value] | 0.08 ± 0.03 [0.01 to 0.15; <0.0001]

Multi-Center, Single-Arm, Open-Label, Long-Term Extension Clinical Trial of PROCYSBI

Forty of the 41 patients completing the randomized trial continued treatment with PROCYSBI in an open-label extension trial, for a total treatment duration ranging from 1 month to 6.7 years in the study (Study RP103-03-04; NCT01197378). Thirty-six of the 40 patients continued treatment with PROCYSBI for at least 24 months and 20 patients continued treatment for longer than 60 months in the extension trial, and maintained their mean WBC cystine concentrations below 1 nmol ½ cystine/mg protein (measured using the mixed leukocyte assay) over this time period.

Thirteen pediatric patients, aged 2 to 6 years, were also enrolled in the extension trial and treated with PROCYSBI. All of them were on treatment with immediate-release cysteamine bitartrate at the time of enrollment. All 13 patients received at least 18 months of treatment with PROCYSBI, and their mean ± SD WBC cystine concentration (measured using the mixed leukocyte assay) decreased from 1.41 ± 1.03 nmol ½ cystine/mg protein at baseline to 1.22 ± 1.40 nmol ½ cystine/mg protein after 18 months of treatment. Seven of these pediatric patients were able to achieve a WBC cystine concentration (measured using the mixed leukocyte assay) of less than 1.0 nmol ½ cystine/mg protein after 18 months of treatment; their mean ± SD dose of PROCYSBI increased from 0.81 ± 0.25 grams/m^2 per day at baseline to 0.90 ± 0.25 grams/m^2 per day after 18 months of treatment.

During extended treatment with PROCYSBI, mean estimates of renal function, as measured by the eGFR, were maintained.

Multi-Center, Open-Label, Clinical Trial in Cysteamine Naïve Patients Less than 6 Years of Age

A clinical trial of PROCYSBI (Study RP103-08; NCT01744782) was conducted in 17 patients with a documented diagnosis of nephropathic cystinosis who were naïve to cysteamine treatment (15 patients between the ages of 1 and 5 years, one 9-year old and one 22-year old). The PROCYSBI starting dose was ¼ the maintenance dose of 1 gram/m^2/day (actual dosing was based on weight bands using the available capsule strengths, as shown in (Table 1) and the dosage was gradually increased by 10% every 2 weeks. Dosage adjustment was allowed throughout the trial and was based on subject-specific factors (e.g., weight, tolerability) and WBC cystine concentrations. WBC cystine concentrations were obtained 30 minutes after the morning dose collected bi-monthly until the patient's WBC cystine concentration (using the mixed leukocyte assay) was < 1 nmol ½ cystine/mg protein. Treatment duration was at least 12 months.

Fourteen of the 15 patients between 1 year and less than 6 years of age completed 12 months of treatment, and 10 patients completed 18 months of treatment. Thirteen of the 14 patients achieved their highest total daily dosage of PROCYSBI following the 9-month visit (9-month visit for 8 subjects, 12-month visit for 4 subjects, and 18-month visit for 1 subject).

Some patients did not have WBC cystine samples collected at each visit or results were not reportable due to laboratory errors. Thus, the numbers of patients with available WBC cystine data varied across the time points analyzed. In patients with missing samples, dose escalation was continued if the patient's last reported WBC cystine concentration was > 1 nmol ½ cystine/mg protein.

In patients 1 year to less than 6 years, the mean (±SD) WBC cystine concentration on Day 1, 30 minutes following the first dose, was 3.17±2.95 nmol ½ cystine/mg protein (n=15 patients). At 12 months (13 patients with samples), the mean WBC cystine concentration was 0.80 ± 0.60 nmol ½ cystine/mg protein at 30 minutes post dose. At 18 months (9 patients with samples) the mean WBC cystine concentration was 0.74 ± 0.64 nmol ½ cystine/mg protein at 30 minutes post dose.

In patients 1 year to less than 6 years, the mean (±SD) weight percentiles at Day 1 (n=14), 12 months (n=13) and 18 months (n=10) were 3.5 ± 11.1, 11.9 ± 18.3, and 30.1 ± 28.2, respectively, and patient weight z-scores were -4.0 ± 2.1, -2.2 ± 1.7, and -1.3 ± 2.0, respectively. In the same patients, similar trends were observed for height.

16 HOW SUPPLIED/STORAGE AND HANDLING

How Supplied

PROCYSBI (cysteamine bitartrate) delayed-release capsules

- 25 mg cysteamine: A hard gelatin capsule with light blue opaque cap imprinted with "PRO" in white ink and light blue opaque body imprinted with "25 mg" in white ink, supplied as bottle of 60 capsules (NDC 75987-100-04). Each bottle contains one desiccant canister and one oxygen absorber canister.
- 75 mg cysteamine: A hard gelatin capsule with dark blue opaque cap imprinted with "PRO" in white ink and light blue opaque body imprinted with "75 mg" in white ink, supplied as bottle of 250 capsules (NDC 75987-101-08). Each bottle contains one desiccant canister and two oxygen absorber canisters.

PROCYSBI (cysteamine bitartrate) delayed-release oral granules

- 75 mg cysteamine: Single-use packets containing white to off-white granules, supplied as 60 packets in a carton (NDC 75987-140-13).
- 75 mg cysteamine: Single-use packets containing white to off-white granules, supplied as 120 packets in a carton (NDC 75987-140-14).
- 300 mg cysteamine: Single-use packets containing white to off-white granules, supplied as 60 packets in a carton (NDC 75987-145-13).
- 300 mg cysteamine: Single-use packets containing white to off-white granules, supplied as 120 packets in a carton (NDC 75987-145-14).

Storage and Handling

- Prior to dispensing, store PROCYSBI delayed-release capsules and PROCYSBI delayed-release oral granules in a refrigerator, 2°C to 8°C (36°F to 46°F).
- Dispense PROCYSBI delayed-release capules and PROCYSBI delayed-release oral granules with a 4 month discard date.
- Dispense in original packaging. Do not subdivide or repackage.
- Do not remove desiccant or oxygen absorber(s) from the bottle of PROCYSBI delayed-release capsules. Keep bottles tightly closed in a dry place.
- Protect from light and moisture.

Instructions for the Patient

- Store PROCYSBI delayed-release capsules and PROCYSBI delayed-relase oral granules at room temperature, 20°C to 25°C (68°F to 77°F) in the original packaging. Do not subdivide or repackage.
- Protect from light and moisture.
- Do not store PROCYSBI delayed-release oral granules in opened packets.

17 PATIENT COUNSELING INFORMATION

Advise the patient to read the FDA-approved patient labeling (Patient Information and Instructions for Use)

Ehlers-Danlos-like Syndrome

Advise patients and caregivers that PROCYSBI may cause abnormalities of the skin, bones, and joints. Advise patients to report any skin changes or problems with their bones or joints to their physician [see Warnings and Precautions (5.1)].

Skin Rash

Advise patients and caregivers to contact their physician immediately if they experience a skin rash [see Warnings and Precautions (5.2)].

Gastrointestinal Ulcers and Bleeding

Advise patients and caregivers that PROCYSBI may cause ulcers and bleeding. Advise patients to contact their physician immediately if they experience stomach pain, nausea, vomiting, loss of appetite, or are vomiting blood [see Warnings and Precautions (5.3)].

Fibrosing Colonopathy

Advise patients and caregivers that fibrosing colonopathy has been reported with PROCYSBI. Advise patients to contact their physician immediately if they experience severe, persistent and/or worsening stomach pain, vomiting, bloody or persistent diarrhea, or inability to control bowel movements [see Warnings and Precautions (5.4)].

Central Nervous System Symptoms

Advise patients and caregivers that PROCYSBI may impair their ability to perform tasks such as driving or operating machinery. Advise patients to contact their physician immediately if they experience seizures, lethargy, somnolence, depression, and encephalopathy [see Warnings and Precautions (5.5)].

Benign Intracranial Hypertension

Advise patients and caregivers that PROCYSBI may cause benign intracranial hypertension. Advise patients to contact their physician immediately if they experience headache, tinnitus, dizziness, nausea, double vision, blurry vision, loss of vision, or eye pain [see Warnings and Precautions (5.7)].

Use by Pregnant Women

Advise patients and to contact their physician immediately if they suspect they may be pregnant. Discuss with the patient the individual risks and benefits of continuing PROCYSBI during pregnancy [see Use in Specific Populations (8.1)].

Breastfeeding

Advise patients that breastfeeding is not recommended while taking PROCYSBI [see Use in Specific Populations (8.2)].

Laboratory Monitoring

Discuss with the patient and caregivers the importance of required laboratory testing to determine the correct dose of PROCYSBI [see Dosage and Administration (2.5)].

Administration

- Advise patients and caregivers to follow the instruction below for taking PROCYSBI.
  Capsules:
  - Swallow PROCYSBI capsules whole. Do not crush or chew capsules or capsule contents.
  - Take PROCYSBI capsules with fruit juice (except grapefruit juice) or water.
  - For patients who cannot swallow the capsules, the capsules can be opened and the capsule contents sprinkled on and mixed in applesauce, berry jelly or fruit juice (except grapefruit juice) and administered orally.
  - For patients with a gastrostomy tube, follow the instructions in the Instructions for Use.
  Oral Granules:
  - Do not crush or chew the granules.
  - Sprinkle and mix intact granules from on applesauce, berry jelly or fruit juice (except grapefruit juice) and administer orally.
  - For patients with a gastrostomy tube, follow the instruction in the Instructions for Use
- Administer PROCYSBI at least 1 hour before or 1 hour after medications containing bicarbonate or carbonate.
- Do not eat for at least 2 hours before and for at least 30 minutes after taking PROCYSBI. If unable to take PROCYSBI without eating, take with food but limit the amount of food to approximately 4 ounces (½ cup) 1 hour before through 1 hour after administration. Avoid high fat food close to dosing of PROCYSBI.
- Avoid drinking alcohol while taking PROCYSBI.
- Take PROCYSBI consistently and to not miss doses. If a dose is missed, take the dose as soon as possible up to 8 hours after the scheduled time. However, if a dose is missed and the next scheduled dose is due in less than 4 hours, do not take the missed dose, and to take the next dose at the usual scheduled time. Do not take 2 doses at one time to make up for a missed dose [see Dosage and Administration (2.6)].

Storage

Advise patients and caregivers to keep PROCYSBI in a dry place. Protect from moisture. For bottles, keep PROCYSBI delayed-release capsules in the original bottle. Do not remove the dessicant or oxygen absorber from the bottle. Do not store PROCYSBI delayed-release oral granules in opened packets [see How Supplied/Storage and Handling (16)].

AMGEN
Horizon Therapeutics USA, Inc.
Deerfield, IL 60015

© 2025 Amgen Inc. All rights reserved.

1XXXXXX-V3

PATIENT INFORMATION
PROCYSBI® (Pro-CIS-bee)
(cysteamine bitartrate)
delayed-release capsules and delayed-release oral granules

What is PROCYSBI?
PROCYSBI is a prescription medicine used to treat nephropathic cystinosis in adults and children 1 year of age and older.
It is not known if PROCYSBI is safe and effective in children under 1 year of age.

Do not take PROCYSBI if you are allergic to penicillamine or cysteamine.

Before taking PROCYSBI, tell your doctor about all of your medical conditions, including if you:

- drink alcohol.
- have a skin rash or bone problems.
- have or have had stomach or bowel (intestinal) problems including ulcers or bleeding.
- have a history of seizures, lack of energy, unusual sleepiness, depression, or changes in your ability to think clearly.
- have liver or blood problems.
- are pregnant or plan to become pregnant. It is not known if PROCYSBI will harm your unborn baby. Tell your doctor right away if you think that you are pregnant. Talk with your doctor about the benefits and risks of taking PROCYSBI during pregnancy.
- are breastfeeding or plan to breastfeed. You should not breastfeed during treatment with PROCYSBI. Talk with your doctor about the best way to feed your baby if you take PROCYSBI.

Tell your doctor about all the medicines you take, including prescription and over-the-counter medicines, vitamins, and herbal supplements.
Know the medicines you take. Keep a list of them to show your doctor and pharmacist when you get a new medicine.

How should I take PROCYSBI?

- Read the "Instructions for Use" that comes with PROCYSBI for information about the right way to prepare and take PROCYSBI.
- Take PROCYSBI exactly as your doctor tells you to.
- Your doctor may start you on a low dose of PROCYSBI and slowly increase your dose to help avoid side effects, especially if you have not taken a medicine that contains cysteamine bitartrate before.
- Do not change your dose of PROCYSBI unless your doctor tells you to.
- PROCYSBI is taken 2 times each day, every 12 hours.
- Take PROCYSBI the same way each time, either without eating or with a small amount of food, as follows:
  - If you take PROCYSBI without eating, do not eat for at least 2 hours before taking PROCYSBI and at least 30 minutes after taking PROCYSBI.
  - If you are not able to take PROCYSBI without eating, you can eat a small amount of food (½ cup) within 1 hour before you take PROCYSBI through 1 hour after you take it.
  - Avoid eating foods that are high in fat close to the time that you will take a dose of PROCYSBI.
- Talk to your doctor or pharmacist if you have questions about how to take PROCYSBI.
- PROCYSBI is available as capsules in a bottle and oral granules in packets.
  Capsules:
  - Swallow PROCYSBI capsules whole. Do not crush or chew capsules or capsule contents.
  - Take the PROCYSBI capsule whole with fruit juice (except for grapefruit juice) or water.
  - If PROSCYBI capsules cannot be swallowed whole, the capsule may be opened and the contents sprinkled on and mixed in applesauce, berry jelly or fruit juice (except grapefruit juice) and taken by mouth.
  - Read the "Instructions for Use" if you have a gastrostomy tube (G-tube).
  Granules:
  - Sprinkle and mix PROCYSBI oral granules on applesauce, berry jelly or fruit juice (except grapefruit juice) and take by mouth. Do not crush or chew oral granules.
  - Read the "Instructions for Use" if you have a gastrostomy tube (G-tube).
- Take PROCYSBI at least 1 hour before or 1 hour after you take medicines that contain bicarbonate or carbonate.
- If you miss a dose, take it as soon as possible, up to 8 hours after the scheduled time of the missed dose. If it is less than 4 hours of the time the next dose is due, skip the missed dose. Take the next dose at your regularly scheduled time. Do not take 2 doses at one time to make up for a missed dose.
- If you take too much PROCYSBI, call your doctor or go to the nearest hospital emergency room right away.
- Your doctor should do blood tests to measure the amount of cystine inside your white blood cells or to measure the amount of PROCYSBI in your blood before you start taking it and regularly during treatment with PROCYSBI. This will help your doctor to prescribe the dose of PROCYSBI that is right for you.
- Take supplements if prescribed by your doctor, such as salt or mineral replacement supplements, vitamin D, or thyroid hormone.

What should I avoid while taking PROCYSBI?

- Do not drive or operate machinery until you know how PROCYSBI affects you. PROCYSBI can make you sleepy or less alert than normal.
- Do not drink alcohol if you take PROCYSBI. Drinking alcohol while taking PROCYSBI may change how PROCYSBI works and may cause an increase in the amount of PROCYSBI in your blood that may cause serious side effects.

What are the possible side effects of PROCYSBI?
PROCYSBI can cause serious side effects, including:

- Skin, bone, and joint problems. People treated with high doses of cysteamine bitartrate may develop abnormal changes of their skin and bones. These changes may include stretch marks, bone injuries (such as fractures), bone deformities, and joint problems. Check your skin while taking PROCYSBI. Tell your doctor if you notice any skin changes or problems with your bones or joints. Your doctor will check you for these problems.
- Skin rash. Skin rash is common with cysteamine bitartrate and may sometimes be severe. Tell your doctor right away if you get a skin rash. Your dose of PROCYSBI may need to be decreased until the rash goes away. If the rash is severe, your doctor may tell you to stop taking PROCYSBI.
- Stomach and bowel (intestinal) problems. Some people who take other medicines that contain cysteamine bitartrate may develop ulcers and bleeding in their stomach or bowel. People treated with PROCYSBI may also develop abnormal swelling and narrowing of the large bowel which must be treated right away. Tell your doctor right away if you get abdominal pain, nausea, vomiting, loss of appetite, weight loss, bloody or persistent diarrhea, or are vomiting blood or have bowel moments that you cannot control.
- Central nervous system symptoms. Some people who take other medicines that contain cysteamine bitartrate develop seizures, depression, and become very sleepy. The medicine may affect how your brain is working (encephalopathy). Tell your doctor right away if you develop any of these symptoms.
- Low white blood cell count and certain abnormal liver function blood tests. Your doctor should check you for these problems.
- Benign intracranial hypertension (pseudotumor cerebri) has happened in some people who take immediate-release cysteamine bitartrate. This is a condition where there is high pressure in the fluid around the brain. Your doctor should do eye examinations to find and treat this problem early.
  Tell your doctor right away if you develop any of the following symptoms while taking PROCYSBI: headache, buzzing or "whooshing" sound in the ear, dizziness, nausea, double vision, blurry vision, loss of vision, pain behind the eye, or pain with eye movement.

The most common side effects with PROCYSBI include:

  - vomiting
  - pink eye
  - tiredness
  - problems with body salts or electrolytes

- nausea
- diarrhea
- flu
- infection of ear, nose or throat

- stomach (abdominal) pain
- cold
- headache
- joint pain

These are not all the possible side effects of PROCYSBI. Call your doctor for medical advice about side effects. You may report side effects to FDA at 1-800-FDA-1088.

General information about the safe and effective use of PROCYSBI.
Medicines are sometimes prescribed for purposes other than those listed in a Patient Information leaflet. Do not use PROCYSBI for a condition for which it was not prescribed. Do not give PROCYSBI to other people, even if they have the same symptoms that you have. It may harm them. You can ask your doctor or pharmacist for information about PROCYSBI that is written for health professionals.

What are the ingredients in PROCYSBI?
Active ingredients: cysteamine bitartrate
Inactive ingredients: Eudragit® L 30 D-55, hypromellose, microcrystalline cellulose, purified water, sodium lauryl sulfate, talc, and triethyl citrate. Capsule shell ingredients: gelatin, titanium dioxide, blue ink and white ink.
Horizon Therapeutics USA, Inc., Deerfield, IL 60015
For more information go to www.PROCYSBI.com or call 1 800 77 AMGEN (1 800 772 6436)

This Patient Information has been approved by the U.S. Food and Drug Administration.

Revised: 12/2024

Instructions for Use PROCYSBI® (Pro-CIS-bee) (cysteamine bitartrate) delayed-release capsules and delayed-release oral granules

PROCYSBI is available as:

- Capsules in bottles (see "Taking PROCYSBI Capsules")
- Oral granules in packets (see "Taking PROCYSBI Oral Granules")

Your doctor will tell you the number of capsules or packets of oral granules you need to take for each dose. If you have any questions, talk to your doctor.

Taking PROCYSBI capsules

PROCYSBI capsules should be swallowed whole with fruit juice (except grapefruit juice) or water. If you cannot swallow the capsule whole, you can open each capsule and take the capsule contents with certain foods and juices, or the capsule contents can be given through a gastrostomy tube (G-tube).

Opening PROCYSBI capsules:

- Do not pinch the PROCYSBI capsule in the center.
- Do not crush or chew the PROCYSBI capsule.
- Use both hands to open the PROCYSBI capsule.
- Hold each end of the PROCYSBI capsule with your thumb and index (pointer) fingers and gently twist the two ends in opposite directions to open.

Taking PROCYSBI with applesauce or berry jelly:

Do not take PROCYSBI with any food other than applesauce or berry jelly.

Step 1: | Place about ½ cup (4 ounces) of applesauce or berry jelly into a clean container. If needed, use a smaller amount you can finish in one feeding. Do not use any other food.
Step 2: | Open the PROCYSBI capsule. See "Opening PROCYSBI capsules" above. You may need to use more than 1 PROCYSBI capsule for the dose prescribed by your doctor.
Step 3: | Sprinkle the granules that are inside the capsule onto the applesauce or berry jelly.
Step 4: | Mix the granules with the applesauce or berry jelly. Do not crush the granules.
Step 5: | Swallow the applesauce or berry jelly and granules mixture within 30 minutes after preparing. Do not chew the granules. Do not save the applesauce or berry jelly and granules for later use.

Taking PROCYSBI with fruit juice:

Do not take PROCYSBI with grapefruit juice.

Step 1: | Pour about ½ cup (4 ounces) of fruit juice into a clean cup.
Step 2: | Open the PROCYSBI capsule. See "Opening PROCYSBI capsules" above. You may need to use more than 1 PROCYSBI capsule for the dose prescribed by your doctor.
Step 3: | Sprinkle all the granules that are inside the capsule into ½ cup (4 ounces) of fruit juice.
Step 4: | Stir gently until mixed. Do not crush the granules.
Step 5: | Drink all of the fruit juice and granules mixture within 30 minutes of mixing. Do not chew the granules. Do not save the fruit juice or water and granules mixture for later use.

Giving PROCYSBI through a gastrostomy tube (G-tube):

It is best to use a straight (bolus) feeding tube.

For people who have a gastrostomy tube (G-tube) that is size 14 French or larger, PROCYSBI may be given as follows:

Use only strained applesauce with no chunks when giving PROCYSBI through a gastrostomy tube (G-tube).

Step 1: | Flush the gastrostomy tube button with 5 mL of water to clear the button.
Step 2: | Place about ½ cup (4 ounces) of applesauce into a clean container. Children who weigh 55 pounds (25 kilograms) or less can take PROCYSBI with at least 1/8 cup (1 ounce) of applesauce.
Step 3: | Open the PROCYSBI capsule. See "Opening PROCYSBI capsules" above. You may need to use more than 1 PROCYSBI capsule for the dose prescribed by your doctor.
Step 4: | Sprinkle the granules that are inside the capsule on the applesauce. Gently mix the granules with the applesauce. Do not crush the granules.
Step 5: | Place the tip of a catheter tip syringe at the bottom of the container of applesauce and granules mixture. For an adult dose, draw up about 40 mL of the mixture. When giving to a child, draw up at least 10 mL of the mixture for doses of 1 or 2 capsules.
Step 6: | Place the tip of the catheter tip syringe into the feeding tube that will be connected to the gastrostomy tube. Fill the feeding tube with the applesauce and granules mixture.
Step 7: | Hold the feeding tube in a horizontal (straight across) position. Give the applesauce and granules mixture through the gastrostomy tube at a quick and steady rate of 10 mL over 10 seconds.
Step 8: | Repeat Step 5 through Step 7 until all of the applesauce and granules mixture is given. Give all of the applesauce and granules mixture through the gastrostomy tube within 30 minutes of mixing. Do not save the applesauce and granules mixture for later use.
Step 9: | Draw up at least 10 mL of fruit juice or water into another catheter tip syringe. Do not use grapefruit juice. Gently swirl the syringe. Flush the gastrostomy tube with the fruit juice or water. Use enough fruit juice or water to flush the gastrostomy tube so that there is no applesauce and granules mixture left in the gastrostomy tube.

Taking PROCYSBI oral granules

You must mix the PROCYSBI oral granules in packets with certain foods and juices to take your PROCYSBI dose. PROCYSBI oral granules can also be given through a gastrostomy tube (G-tube).

Opening PROCYSBI oral granules in packets:

- Tear open the packet along the dotted (perforated) line.
- Do not store granules in opened packets for your next dose.

Taking PROCYSBI with applesauce or berry jelly:

Do not take PROCYSBI with any food other than applesauce or berry jelly.

Step 1: | Place about ½ cup (4 ounces) of applesauce or berry jelly into a clean container. Do not use any other food.
Step 2: | Open the packet of PROCYSBI oral granules. See "Opening PROCYSBI oral granules in packets" above. You may need to use more than 1 packet of PROCYSBI oral granules for the dose prescribed by your doctor.
Step 3: | Sprinkle all the granules that are inside the packet onto the applesauce or berry jelly.
Step 4: | Mix the granules with the applesauce or berry jelly. Do not crush the granules.
Step 5: | Swallow the applesauce or berry jelly and granules mixture within 30 minutes after preparing. Do not chew the granules. Do not save the applesauce or berry jelly and granules for later use.

Taking PROCYSBI with fruit juice:

Do not take PROCYSBI with grapefruit juice.

Step 1: | Pour about ½ cup (4 ounces) of fruit juice into a clean cup.
Step 2: | Open the PROCYSBI packet. See "Opening PROCYSBI oral granules in packets" above. You may need to use more than 1 packet of PROCYSBI oral granules for the dose prescribed by your doctor.
Step 3: | Sprinkle all the granules that are inside the packet into ½ cup (4 ounces) of fruit juice.
Step 4: | Stir gently until mixed. Do not crush the granules.
Step 5: | Drink all of the fruit juice and granules mixture within 30 minutes of mixing. Do not chew the granules. Do not save the fruit juice and granules for later use.

Giving PROCYSBI through a gastrostomy tube (G-tube):

It is best to use a straight (bolus) feeding tube.

For people who have a gastrostomy tube (G-tube) that is size 14 French or larger, PROCYSBI may be given as follows:

Use only strained applesauce with no chunks when giving PROCYSBI through a gastrostomy tube (G-tube).

Step 1: | Flush the gastrostomy tube button with 5 mL of water to clear the button.
Step 2: | Place about ½ cup (4 ounces) of applesauce into a clean container. Children who weigh 55 pounds (25 kilograms) or less can take PROCYSBI with at least 1/8 cup (1 ounce) of applesauce.
Step 3: | Open the packet of PROCYSBI oral granules. See "Opening PROCYSBI oral granules in packets" above. You may need to use more than 1 packet of PROCYSBI oral granules for the dose prescribed by your doctor.
Step 4: | Sprinkle all the granules that are inside the packet on the applesauce. Gently mix the granules with the applesauce. Do not crush the granules.
Step 5: | Place the tip of a catheter tip syringe at the bottom of the container of applesauce and granules mixture. For an adult dose, draw up about 40 mL of the mixture. When giving to a child, draw up at least 10 mL of the mixture for doses of 1 or 2 packets.
Step 6: | Place the tip of the catheter tip syringe into the feeding tube that will be connected to the gastrostomy tube. Fill the feeding tube with the applesauce and granules mixture.
Step 7: | Hold the feeding tube in a horizontal (straight across) position. Give the applesauce and granules mixture through the gastrostomy tube at a quick and steady rate of 10 mL over 10 seconds.
Step 8: | Repeat Step 5 through Step 7 until all of the applesauce and granules mixture is given. Give all of the applesauce and granules mixture through the gastrostomy tube within 30 minutes of mixing. Do not save the applesauce and granules mixture for later use.
Step 9: | Draw up at least 10 mL of fruit juice into another catheter tip syringe. Do not use grapefruit juice. Gently swirl the syringe. Flush the gastrostomy tube with the fruit juice. Use enough fruit juice to flush the gastrostomy tube so that there is no applesauce and granules mixture left in the gastrostomy tube.

How should I store PROCYSBI?

- Store PROCYSBI capsules and PROCYSBI oral granules at room temperature between 68°F to 77°F (20°C to 25°C).
- Keep PROCYSBI in the original packaging. Do not put PROCYSBI in another container (repackage).
- Keep PROCYSBI in a dry place to protect from moisture.
- The PROCYSBI bottle contains a desiccant to help keep the medicine dry (protect it from moisture). Do not remove the desiccant from the bottle.
- Protect from light.
- Do not store opened packets of PROCYSBI oral granules for later use.
- Throw away (dispose of) any unused PROCYSBI by the "discard after" date on the bottle or carton.

Keep PROCYSBI and all medicines out of the reach of children.

This Instructions for Use has been approved by the U.S. Food and Drug Administration.

Horizon Therapeutics USA, Inc., Deerfield, IL 60015

Revised: December 2024

PRINCIPAL DISPLAY PANEL - 25 mg Capsule Bottle Label

NDC # 75987-100-04

Dispense only in
original packaging

25 mg

PROCYSBI®
(cysteamine bitartrate)
delayed-release capsules

60 capsules

Rx Only

Horizon Therapeutics USA, Inc.
Deerfield, IL 60015
© 2025 Amgen Inc. All rights reserved.
Country of origin: Italy

Discard after:

AMGEN

PRINCIPAL DISPLAY PANEL - 75 mg Capsule Bottle Label

NDC # 75987-101-08

Dispense only in
original packaging

75 mg

PROCYSBI®
(cysteamine bitartrate)
delayed-release capsules

Rx Only

250 capsules

Horizon Therapeutics USA, Inc.
Deerfield, IL 60015
© 2025 Amgen Inc. All rights reserved.
Country of origin: Italy

PRINCIPAL DISPLAY PANEL - 75 mg Granule Packet Carton

NDC: 75987-140-13

PROCYSBI®
(cysteamine bitartrate)
delayed-release oral granules

75 mg

Dispense only in original packaging

Contains 60 packets

Rx Only

PRINCIPAL DISPLAY PANEL - 300 mg Granule Packet Carton

NDC: 75987-145-13

PROCYSBI®
(cysteamine bitartrate)
delayed-release oral granules

300 mg

Dispense only in original packaging

Contains 60 packets

Rx Only